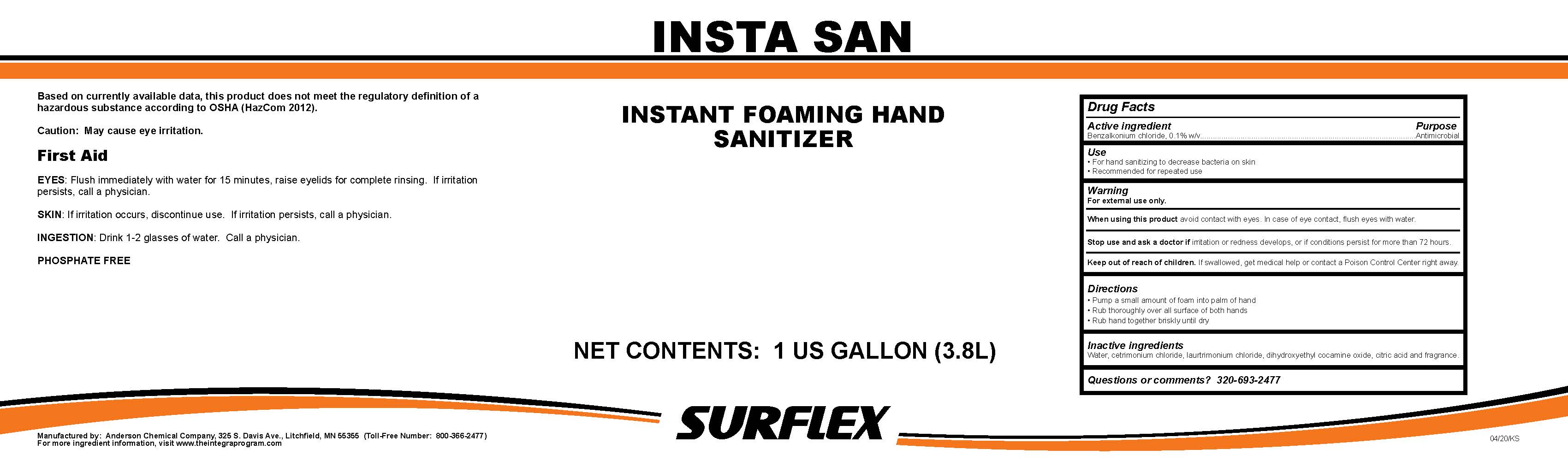 DRUG LABEL: Insta San
NDC: 63131-1134 | Form: LIQUID
Manufacturer: Anderson Chemical Company
Category: otc | Type: HUMAN OTC DRUG LABEL
Date: 20200624

ACTIVE INGREDIENTS: BENZALKONIUM CHLORIDE 1 mg/1 mL
INACTIVE INGREDIENTS: .BETA.-CITRONELLOL, (+/-)-; BUTYLATED HYDROXYANISOLE; LAURTRIMONIUM CHLORIDE; CETRIMONIUM CHLORIDE; WATER; DIHYDROXYETHYL COCAMINE OXIDE; CITRAL; LINALOOL, (+/-)-

Active Ingredient

Benzalkonium chlorinde, 0.1% w/v

Purpose

Antimicrobial

Use

- For hand sanitizing to decrease bacteria on skin.
- Recommended for repeated use.

Warning

For external use only.

When using this product avoid contact with eyes. In case of eye contat, flush eyes with water.

Stop use and ask a doctor if irritation or redness develops, or if conditions perist for more that 72 hours.

Keep out of reach of children. If swallowed, get medical help or contact a poison control center right away.

Directions

▪ Pump a small amount of foam into palm of hand

▪ Rub thoroughly over all surfaces of both hands

▪ Rub hands together briskly until dry

INACTIVE INGREDIENT

Water, dihydroxypropyl PEG-5 linoleammonium chloride, glycereth-2 cocoate, behentrimonium chloride, dihydroxyethyl cocamine oxide, fragrance

Questions

Question or comments? 320-693-2477

First Aid

Eye contact: Flush immediately with plenty of water for 15 minutes. Lift upper and lower eyelids for
complete rinsing. If irritation persists after rinsing, get medical attention.
Skin Contact: If irritation occurs, discontinue use. If irritation persists, call a physician.
Ingestion: Drink 1 or 2 glasses of water. Call a physician.

Directions

▪ Pump a small amount of foam into palm of hand

▪ Rub thoroughly over all surfaces of both hands

▪ Rub hands together briskly until dry